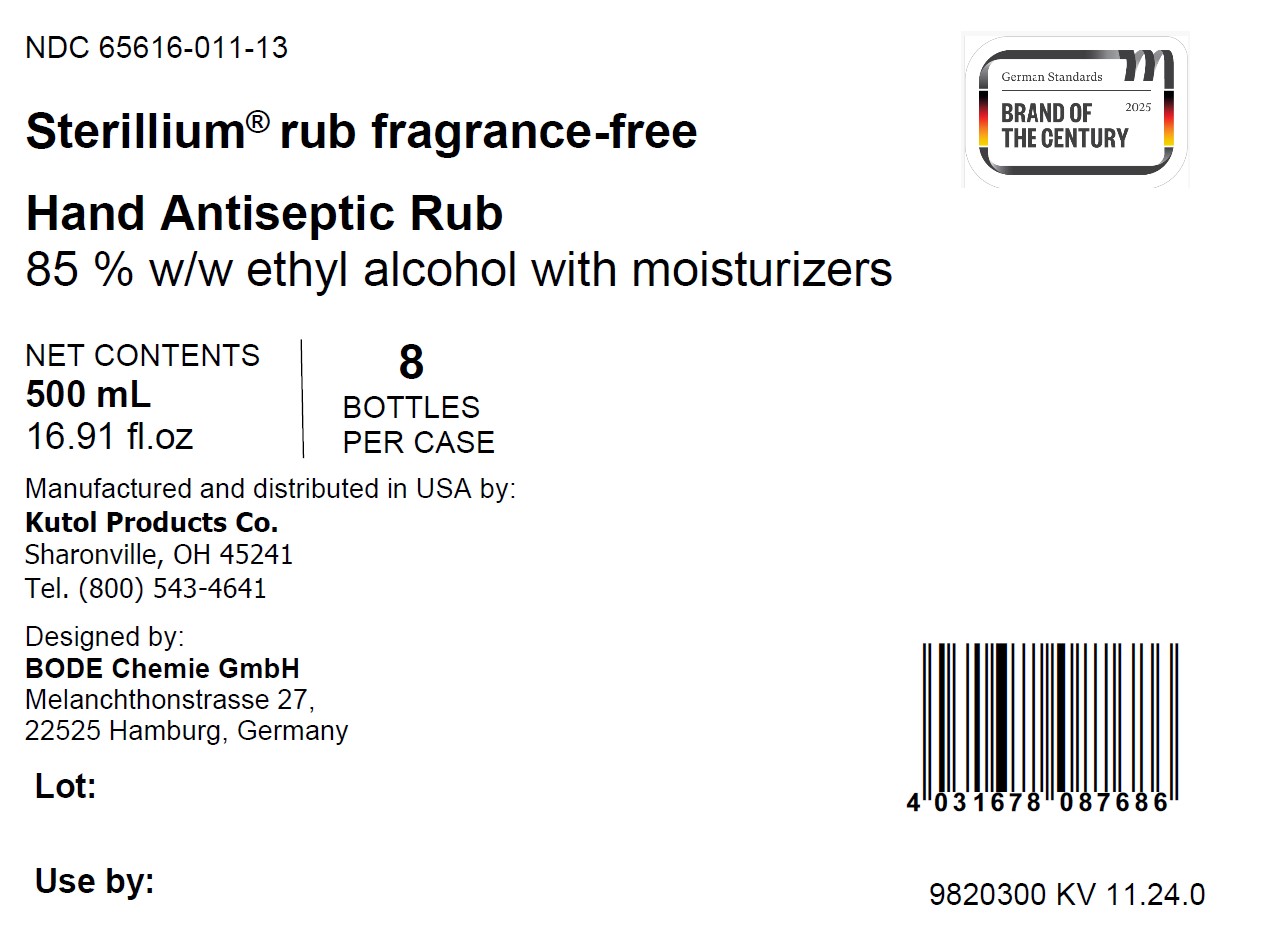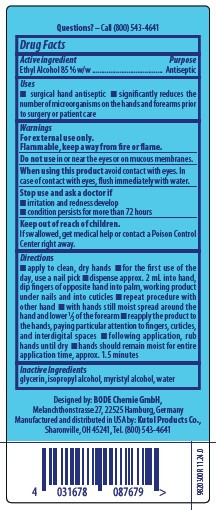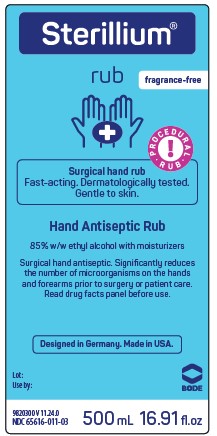 DRUG LABEL: Sterillium rub fragrance-free
NDC: 65616-011 | Form: LIQUID
Manufacturer: BODE Chemie GmbH
Category: otc | Type: HUMAN OTC DRUG LABEL
Date: 20250115

ACTIVE INGREDIENTS: ALCOHOL 89.5 mL/100 mL
INACTIVE INGREDIENTS: GLYCERIN; MYRISTYL ALCOHOL; WATER; ISOPROPYL ALCOHOL

65616-011

Active ingredient

Ethyl Alcohol 85% w/w

Purpose

Antiseptic

Uses

• surgical hand antiseptic

• significantly reduces the number of microorganisms on the hands and forearms prior to surgery or patient care

Warnings

For external use only.

Flammable, keep away from fire or flame.

Do not use in or near the eyes or on mucous membranes.

When using this product avoid contact with eyes. In case of contact with eyes, flush immediately with water.

Stop use and ask a doctor if

• irritation and redness develop

• condition persists for more than 72 hours

Keep out of reach of children.

If swallowed, get medical help or contact a Poison Control Center right away.

Directions

• apply to clean, dry hands

• for the first use of the day, use a nail pick

• dispense approx. 2 mL into hand, dip fingers of opposite hand into palm, working product under nails and into cuticles

• repeat procedure with other hand

• with hands still moist spead around the hand and lower 1/3 of the forearm

• reapply the product to the hands, paying particular attention to fingers, cuticles, and interdigital spaces

• following application, rub hands until dry

• hands should remain moist for entire application time, approx. 1.5 minutes

Inactive Ingredients

glycerin, isopropyl alcohol, myristyl alcohol, water

PACKAGE LABEL

Sterillium

rub

fragrance-free

PROCEDURAL RUB

Surgical hand rub

Fast-acting. Dermatologically tested.

Gentle to skin.

Hand Antiseptic Rub

85% w/w ethyl alcohol with moisturizers

Surgical hand antiseptic. Significantly reduces

the number of microorganisms on the hands

and forearms prior to surgery or patient care.

Read drug facts panel before use.

Designed in Germany. Made in USA.

Lot:

Use by:

BODE

NDC 65616-011-03

500 mL 16.91 fl. oz